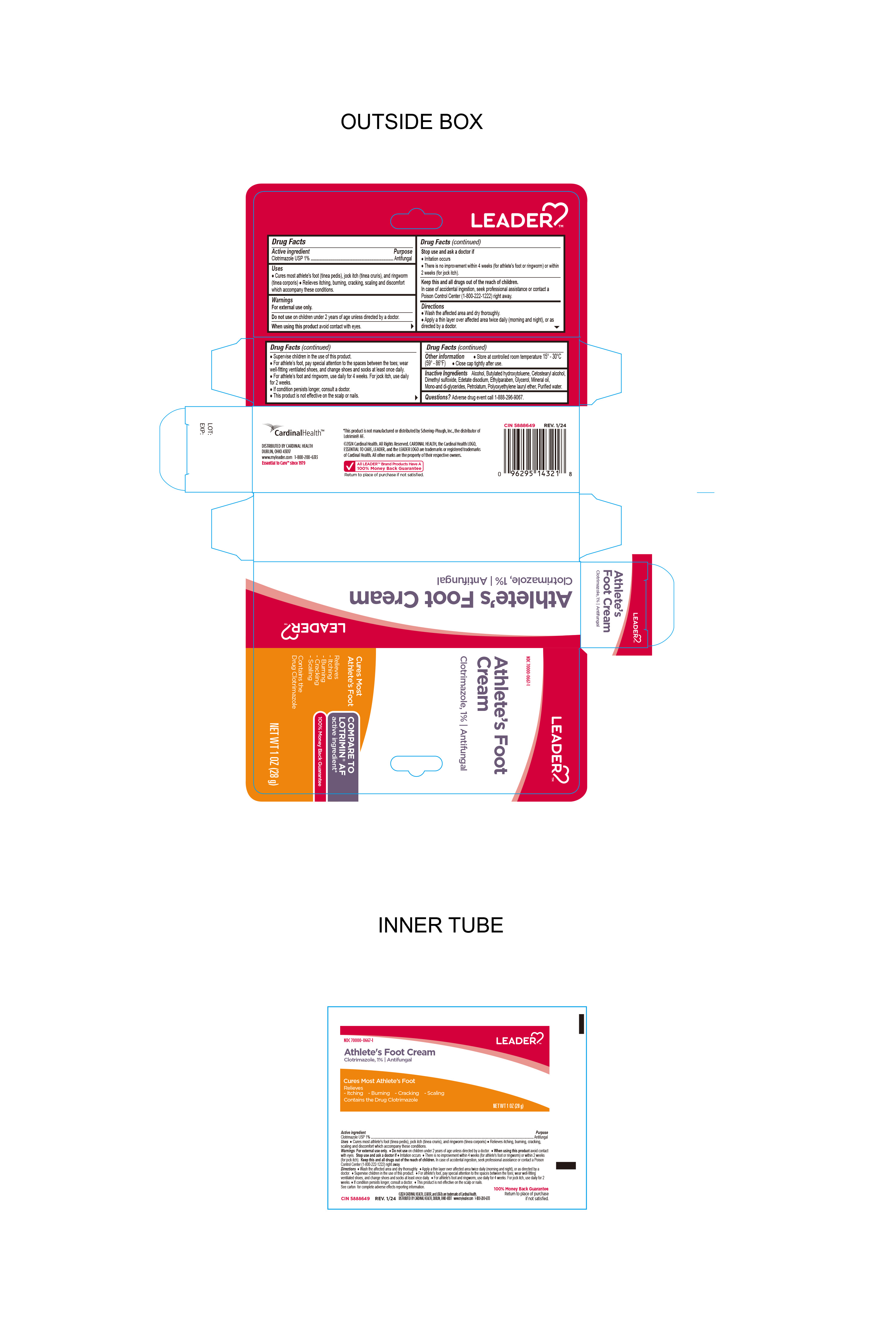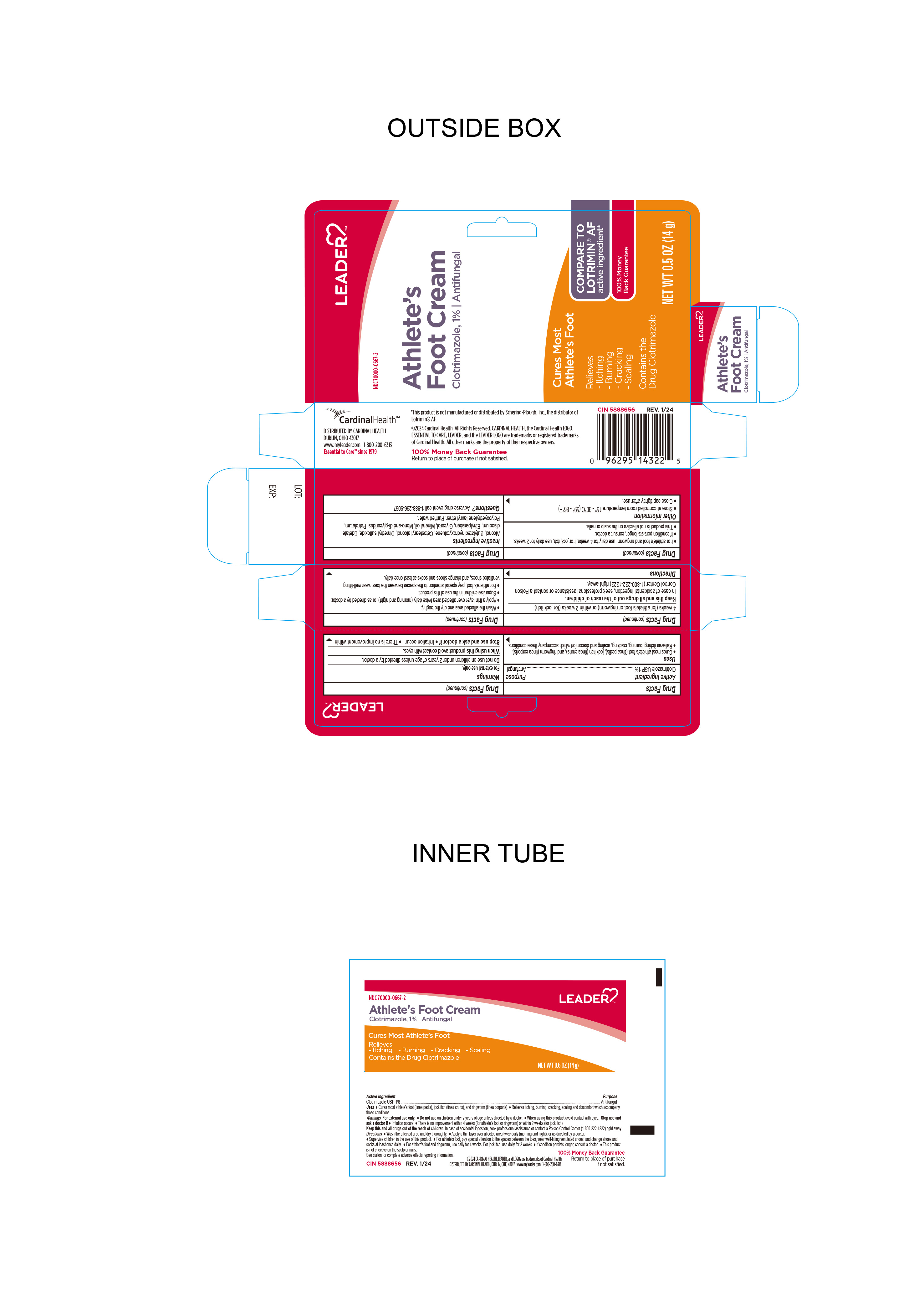 DRUG LABEL: Clotrimazole
NDC: 70000-0667 | Form: CREAM
Manufacturer: Cardinal Health 110 dba LEADER
Category: otc | Type: HUMAN OTC DRUG LABEL
Date: 20240529

ACTIVE INGREDIENTS: CLOTRIMAZOLE 1 g/100 g
INACTIVE INGREDIENTS: MINERAL OIL; DIMETHYL SULFOXIDE; ETHYLPARABEN; GLYCERIN; LAURETH-23; PETROLATUM; WATER; EDETATE DISODIUM; GLYCERYL MONO AND DIPALMITOSTEARATE; BUTYLATED HYDROXYTOLUENE; ALCOHOL; CETOSTEARYL ALCOHOL

Leader Clotrimazole 1% antifungal Athlete's Foot Cream

Active ingredient

Clotrimazole USP 1%

Purpose

Antifungal Cream

Uses

Cures athlete’s foot (tinea pedis), jock itch (tinea cruris), ringworm (tinea corporis). Relieves the itching, burning, cracking, scaling and discomfort which accompany these conditions.

Warnings

For External use only.

Keep this and all drugs out of the reach of children.In case of accidental ingestion, seek professional assistance or contact a Poison Control Center (1-800-222-1222) right away.

Do not use on children under 2 years of age unless direcgted by a doctor

When using this product avoid contact with eyes

Stop use and ask doctor if

- irritaion occurs
- There is no improvement within 4 weeks (for athlete's foot or ringworm) or within 2 weeks (for jock itch).

Directions

- Wash the affected area and dry thoroughly.

● Apply a thin layer oover affected area twice daily (morning and night), or as directed by a doctor.

● Supervise children in the use of this product.

● For athlete’s foot, pay special attention to the spaces between the toes; wear well-fitting ventilated shoes, and change shoes and socks at least once daily.

● For athlete’s foot and ringworm, use daily for 4 weeks. For jock itch, use daily for 2 weeks.

● If conditions persists longer, consult a doctor.

● This product is not effective on the scalp or nails.

Other Information

- store at controlled room temperature 15°-30°C (59°- 86°F)
- Close cap tightly after use.

Inactive Ingredients

Dimethyl Sulfoxide, Ethylparaben, Glycerol, Polyoxyethylene lauryl ether, Mineral Oil, Petrolatum, Water, alcohol, Mono and di-glycerides, Cetostearyl alcohol, edetate disodium, Butylated Hydroxytoluene.

Questions?

Adverse drug event call 1-888-296-9067

Distributed by Cardinal Health

Dublin, Ohio 43017

www.myleader.com

1-800-200-6313

* This product is not manufactured or distributed by Schering-Plough, Inc., the distributor of Lotrimin®AF.

©2024 Cardinal Health. All rights Reserved. CARDINAL HEALTH, the Cardinal Health LOGO ESSENTIAL TO CARE, LEADER, and the LEADER LOGO are trademarks or registered trademarks of Cardinal Health. All other marks are the property of their respective owners.

CIN 5888649